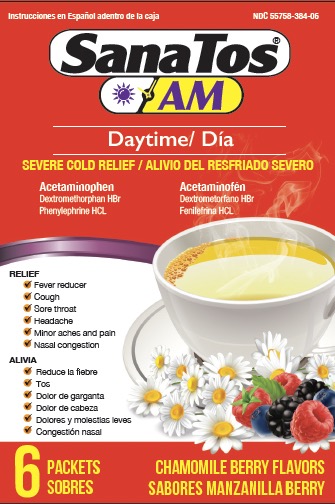 DRUG LABEL: SanaTos
NDC: 55758-384 | Form: GRANULE, FOR SOLUTION
Manufacturer: Pharmadel LLC
Category: otc | Type: HUMAN OTC DRUG LABEL
Date: 20260115

ACTIVE INGREDIENTS: ACETAMINOPHEN 650 mg/1 1; DEXTROMETHORPHAN HYDROBROMIDE 20 mg/1 1; PHENYLEPHRINE HYDROCHLORIDE 10 mg/1 1
INACTIVE INGREDIENTS: ISOPROPYL ALCOHOL; ACESULFAME POTASSIUM; ASPARTAME; ANHYDROUS CITRIC ACID; FD&C BLUE NO. 1; FD&C RED NO. 40; MALTODEXTRIN; SILICON DIOXIDE; SODIUM CITRATE; SUCROSE; TRIBASIC CALCIUM PHOSPHATE; WATER

SanaTos Daytime CB Powder (AS)

Drug Facts

Active Ingredients & Purposes

PURPOSE

Active ingredients (in each packet) | Purposes
Acetaminophen 650 mg | Pain reliever/ fever reducer
Dextromethorphan HBr 20 mg | Cough suppressant
Phenylephrine HCI 10 mg | Nasal decongestant

Uses

Temporarily relieves common cold/flu symptoms:

- minor aches & pains
- sore throat
- headache
- nasal congestion
- cough due to minor throat & bronchial irritation
- and temporarily reduces fever

Warnings

Liver warning: This product contains acetaminophen. Severe liver damage may occur if you take

- more than 6 packets in 24 hours, which is the maximum daily amount
- with other drugs containing acetaminophen
- 3 or more alcoholic drinks every day while using this product

Allergy alert: Acetaminophen may cause severe skin reactions. Symptoms may include:  skin reddening  blisters  rash. If a skin reaction occurs, stop use and seek medical help right away.

Sore throat warning: if sore throat is severe, persists for more than 2 days, is accompanied or followed by fever, headache, rash, nausea, or vomiting, consult a doctor promptly.

Do not use

- with any other drug containing acetaminophen (prescription or nonprescription). If you are not sure whether a drug contains acetaminophen, ask a doctor or pharmacist.
- if you are now taking a prescription monoamine oxidase inhibitor (MAOI) (certain drugs for depression, psychiatric or emotional conditions, or Parkinson's disease), or for 2 weeks after stopping the MAOI drug. If you do not know if your prescription drug contains an MAOI, ask a doctor or pharmacist before taking this product.

Ask a doctor before use if you have

- liver disease
- heart disease
- high blood pressure
- thyroid disease
- diabetes
- a cough that is accompanied by excessive phlegm (mucus)
- a persistent or chronic cough as occurs with smoking, asthma, chronic bronchitis, or emphysema
- difficulty urinating due to enlarged prostate gland

Ask a doctor or pharmacist before use if you are

- taking the blood thinning drug warafin

When using this product

- do not exceed recommended dosage

Stop use and ask a doctor if

- nervousness, dizziness, or sleeplessness occur
- redness or swelling is present
- pain or nasal congestion gets worse or lasts more than 7 days
- fever gets worse or lasts more than 3 days
- any new symptoms occur

If pregnant or breast-feeding,

ask a health care professional before use.

Kepp out of reach of children.

In case of accidental overdose, get medical help or contact a Poison Control Center right away. Prompt medical attention is critical for adults as well as for children even if you do not notice any signs or symptoms.

Directions

- dissolve one packet in an 8 fl oz glass of hot water. If using a microwave; add content into a glass of cool water and stir briskly before and after heating. Do not overheat.
- Sip while hot and consume the entire drink within 10-15 minutes
- a dults and children 12 years of age and older: one (1) packet every 4 hours, do not exceed 6 packets per 24 hours
- children under 12 years of age: do not use

Other information

- each packet contains: potassium 10 mg, sodium 27 mg
- phenylketonurics: contains phenylalanine 13 mg per packet
- store at room temperature 68-77°F (20-25°C)
- do not use if packets are punctured or torn.

Inactive ingredients

acesulfame potassium, anhydrous citric acid, aspartame, chamomile berry flavors, FD&C blue 1, FD&C red 40, isopropyl alcohol, maltodextrin, silicon dioxide, sodium citrate, sucrose, tribasic calcium phosphate, water

Questions?

+1-866-359-3478 (M-F) 9 AM to 5 PM EST or www.pharmadel.com

Distributed by:

PHARMADEL LLC

New Castle, DE 19270

Made in India